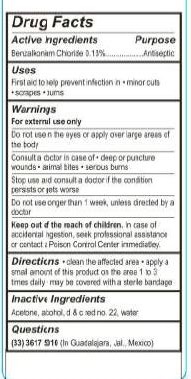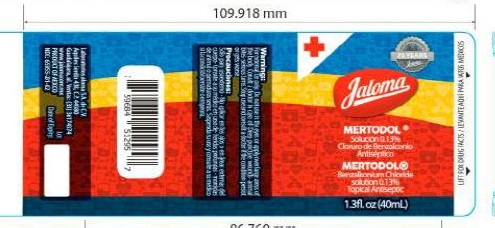 DRUG LABEL: Mertodol Solution
NDC: 65055-201 | Form: LIQUID
Manufacturer: Laboratorios Jaloma, S.A. de C.V.
Category: otc | Type: HUMAN OTC DRUG LABEL
Date: 20231109

ACTIVE INGREDIENTS: BENZALKONIUM CHLORIDE 0.13 g/100 mL
INACTIVE INGREDIENTS: ACETONE; WATER; D&C RED NO. 22

Mertodol solution

Active Ingridients

Benzalkonium Chloride 0.13%

Purpose

Antiseptic

Uses

First aid to help prevent infection in *minor cuts *scrapes *burns

Warnings

-For external use only

-Do not use in the eyes or apply over large areas of the body

Consult a doctor in case of

- deep or puncture wounds

-animal bites

-serious burns

-Stop use and consult a doctor if the condition persist or gets worse

-do not use longer than 1 week, unless directed by a doctor

Keep out of the reach of children.

In case of accidental ingestion, seek professional assistance or contact a Poison Control Center immediatley.

Directions.

-Clean the affected area

-Apply a small amount of this product on the area 1 to 3 times daily

- May be covered with a sterile bandage

Inactive Ingredients

Acetone, Alcohol, d & c red No. 22, water.